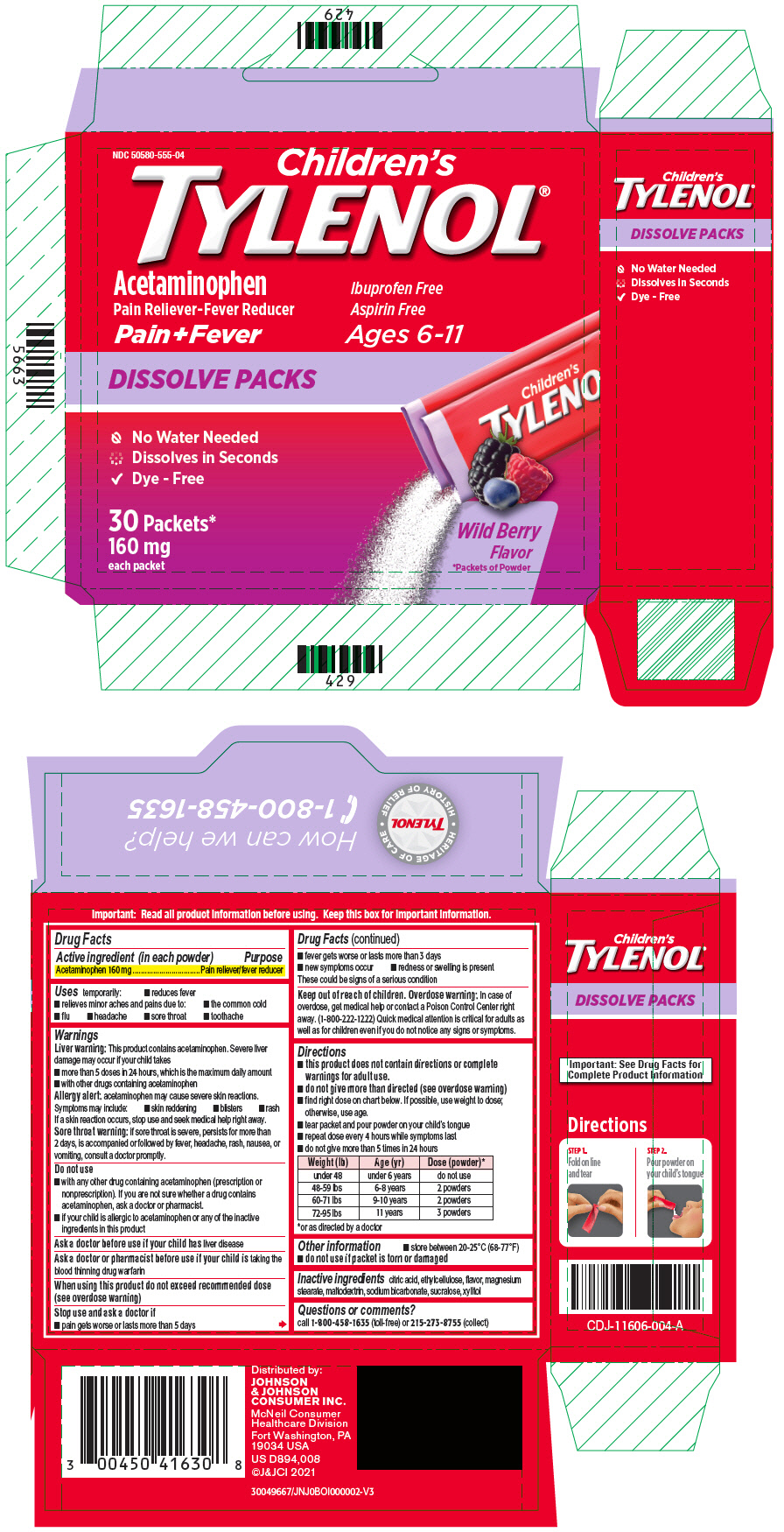 DRUG LABEL: Childrens TYLENOL
NDC: 50580-555 | Form: POWDER
Manufacturer: Kenvue Brands LLC
Category: otc | Type: HUMAN OTC DRUG LABEL
Date: 20250917

ACTIVE INGREDIENTS: ACETAMINOPHEN 160 mg/1 1
INACTIVE INGREDIENTS: ANHYDROUS CITRIC ACID; ETHYLCELLULOSE, UNSPECIFIED; MAGNESIUM STEARATE; MALTODEXTRIN; SODIUM BICARBONATE; SUCRALOSE; XYLITOL

Children's TYLENOL

Drug Facts

Active ingredient (in each powder)

Acetaminophen 160 mg

Purpose

Pain reliever/fever reducer

Uses

temporarily:

- reduces fever
- relieves minor aches and pains due to:
  - the common cold
  - flu
  - headache
  - sore throat
  - toothache

Warnings

Liver warning

This product contains acetaminophen. Severe liver damage may occur if your child takes

- more than 5 doses in 24 hours, which is the maximum daily amount
- with other drugs containing acetaminophen

Allergy alert: acetaminophen may cause severe skin reactions. Symptoms may include:

- skin reddening
- blisters
- rash

If a skin reaction occurs, stop use and seek medical help right away.

Sore throat warning: if sore throat is severe, persists for more than 2 days, is accompanied or followed by fever, headache, rash, nausea, or vomiting, consult a doctor promptly.

Do not use

- with any other drug containing acetaminophen (prescription or nonprescription). If you are not sure whether a drug contains acetaminophen, ask a doctor or pharmacist.
- if your child is allergic to acetaminophen or any of the inactive ingredients in this product

Ask a doctor before use if your child has liver disease

Ask a doctor or pharmacist before use if your child is taking the blood thinning drug warfarin

When using this product do not exceed recommended dose (see overdose warning)

Stop use and ask a doctor if

- pain gets worse or lasts more than 5 days
- fever gets worse or lasts more than 3 days
- new symptoms occur
- redness or swelling is present

These could be signs of a serious condition

Keep out of reach of children.

Overdose warning

In case of overdose, get medical help or contact a Poison Control Center right away. (1-800-222-1222) Quick medical attention is critical for adults as well as for children even if you do not notice any signs or symptoms.

Directions

- this product does not contain directions or complete warnings for adult use.
- do not give more than directed (see overdose warning)
- find right dose on chart below. If possible, use weight to dose; otherwise, use age.
- tear packet and pour powder on your child's tongue
- repeat dose every 4 hours while symptoms last
- do not give more than 5 times in 24 hours

Weight (lb) | Age (yr) | Dose (powder) [or as directed by a doctor]
under 48 | under 6 years | do not use
48-59 lbs | 6-8 years | 2 powders
60-71 lbs | 9-10 years | 2 powders
72-95 lbs | 11 years | 3 powders

Other information

- store between 20-25°C (68-77°F)
- do not use if packet is torn or damaged

Inactive ingredients

citric acid, ethylcellulose, flavor, magnesium stearate, maltodextrin, sodium bicarbonate, sucralose, xylitol

Questions or comments?

call 1-800-458-1635 (toll-free) or 215-273-8755 (collect)

PRINCIPAL DISPLAY PANEL

NDC 50580-555-04

Children's
TYLENOL®

Acetaminophen
Pain Reliever-Fever Reducer

Ibuprofen Free
Aspirin Free

Pain+Fever
Ages 6-11

DISSOLVE PACKS

No Water Needed
Dissolves in Seconds
Dye - Free

30 Packets*
160 mg
each packet

Wild Berry
Flavor

*Packets of Powder